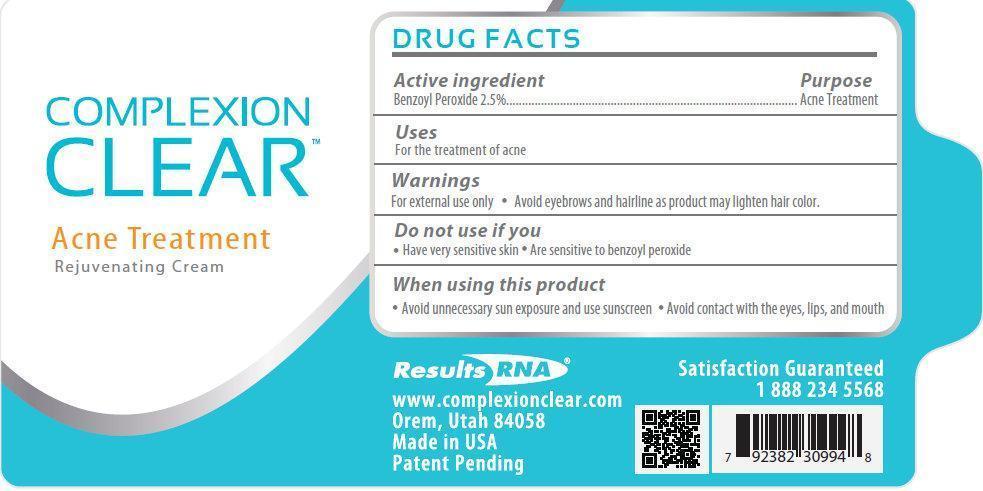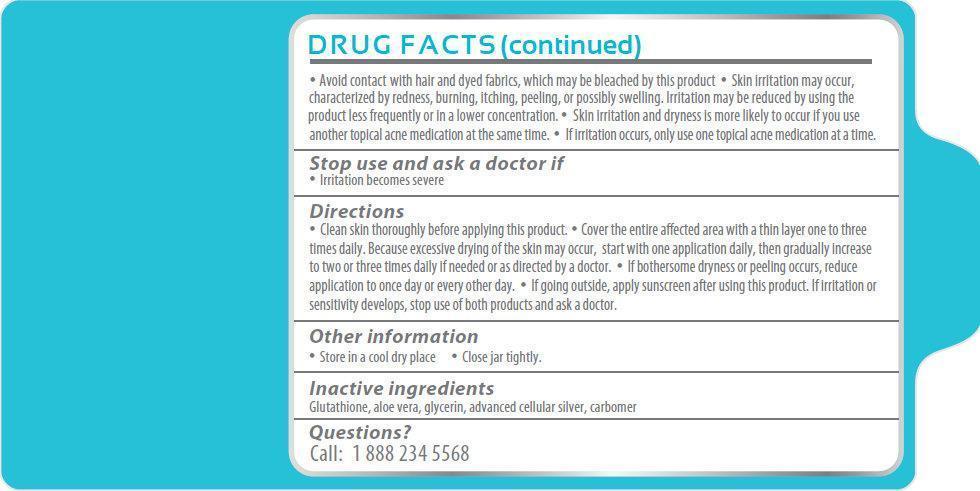 DRUG LABEL: Complexion Clear Acne Treatment Rejuvenating
NDC: 42876-003 | Form: CREAM
Manufacturer: Results RNA, LLC
Category: otc | Type: HUMAN OTC DRUG LABEL
Date: 20121114

ACTIVE INGREDIENTS: BENZOYL PEROXIDE 25 mg/1 mL
INACTIVE INGREDIENTS: GLUTATHIONE; ALOE VERA LEAF; GLYCERIN; SILVER

Complexion Clear Acne Treatment Rejuvenating Cream

Active Ingredient

Benzoyl Peroxide 2.5%

Purpose

Acne Treatment

Uses

For the treatment of acne

Warnings

- For external use only
- Avoid eyebrows and hairline as product may lighten hair color.

Do not use if you

- Have very sensitive skin
- Are sensitive to benzoyl peroxide

When using this product

- Avoid unnecessary sun exposure and use sunscreen
- Avoid contact with the eyes, lips and mouth
- Avoid contact with hair and dyed fabrics, which may be bleached by this product.
- Skin irritation may occur,haracterized by redness, burning, itching, peeling, or possibly swelling. Irritation may be reduced by using the product less frequently or in a lower concentration.
- Skin irritation and dryness is more likely to occur if you use another topical acne medication at the same time.
- If irritation occurs, only use one topical acne medication at a time.

Stop use and ask a doctor if

- Irritation becomes severe

Directions

- Clean skin thoroughly before applying this product.
- Cover the entire affected area with a thin layer one to three times daily. Because excessive drying of the skin may occur, start with one application daily, then gradually increase to two or three times daily if needed or as directed by a doctor.
- If bothersome dryness or peeling occurs, reduce application to once day or every other day.
- If going outside, apply sunscreen after using this product. If irritation or sensitivity develops, stop use of both products and ask a doctor.

Other Information

- Store in a cool dry place
- Close jar tightly

Inactive Ingredients

Glutathione, aloe vera, glycerin, advanced cellular silver, carbomer

Questions?

Call: 1 888 234 5568

Results RNA
www.complexion clear.com
Orem, Utah 84058
Made in USA
Patent Pending
Satisfaction Guaranteed
1 888 823 3869